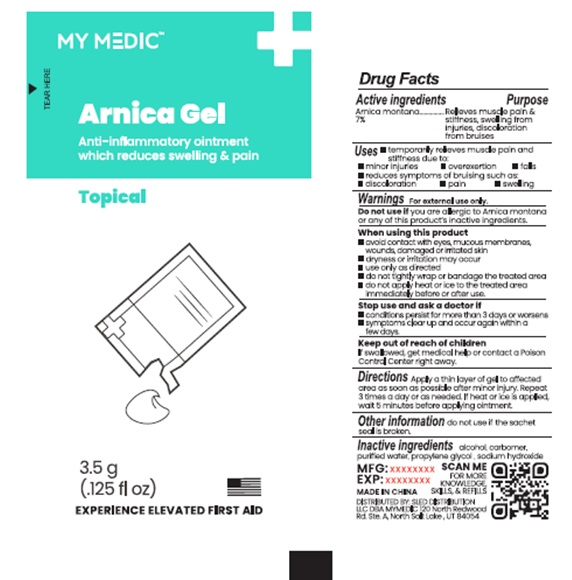 DRUG LABEL: Arnica Gel
NDC: 81417-005 | Form: GEL
Manufacturer: Sled Distribution, LLC
Category: homeopathic | Type: HUMAN OTC DRUG LABEL
Date: 20240115

ACTIVE INGREDIENTS: ARNICA MONTANA 7 g/100 g
INACTIVE INGREDIENTS: ALCOHOL; CARBOMER INTERPOLYMER TYPE A (ALLYL SUCROSE CROSSLINKED); WATER; SODIUM HYDROXIDE; PROPYLENE GLYCOL

81417-005 MY MEDIC ARNICA GEL

Active ingredients:

Arnica montana 7%

Purpose

Relieves muscle pain and stiffness, swelling from injuries, discoloration from bruises.

INDICATIONS AND USAGE

Uses Temporarily relieves muscle pain and stiffness due to:

- minor injuries
- overexertion
- falls
- reduces symptoms of bruising such as : discoloration, pain, swelling.

Warnings For external use only.

Do not use if you are allergic to Arnica montana or any of this product's inactive ingredients.

When using this product

- avoid contact with eyes, mucous membranes, wounds, damaged or irritated skin
- dryness or irritation may occur
- use only as directed
- do not tightly wrap or bandage the treated area
- do not apply heat or ice to the treated area immediately before or after use.

Stop use and ask a doctor if

- Conditions persist for more than 3 days or worsens
- Symptoms clear up and occur again within a few days.

Keep out of reach of children

- If swallowed, get medical help or contact a Poison Control Center immediately.

Directions

Apply a thin layer of gel to affected area as soon as possible after minor injury. Repeat 3 times a day or as needed. lf heat or ice is applied, wait 5 minutes before applying ointment.

Other information do not use if the sachet seal is broken.

INACTIVE INGREDIENT

Alcohol, carbomer, purified water, propylene glycol, sodium hydroxide